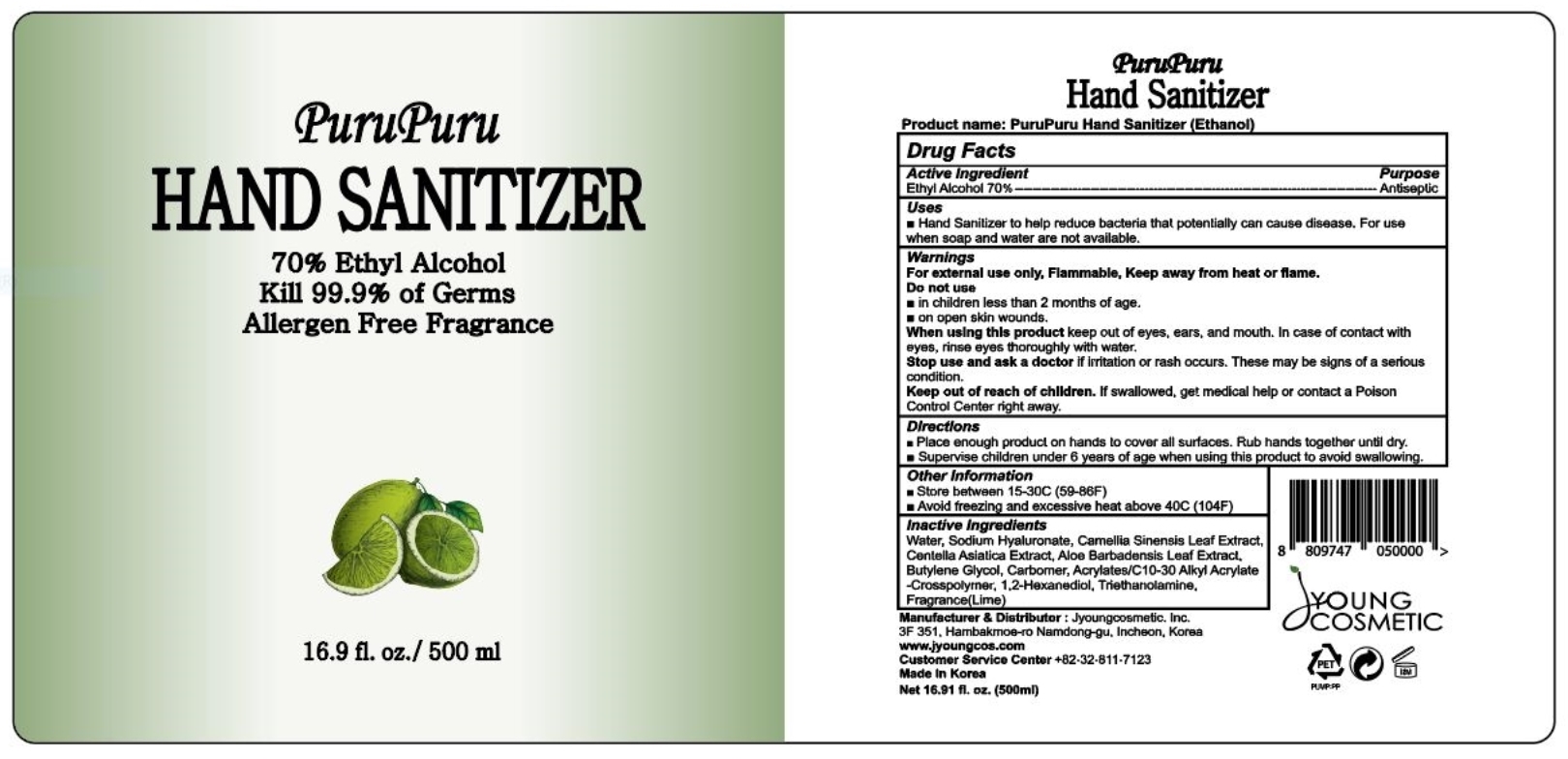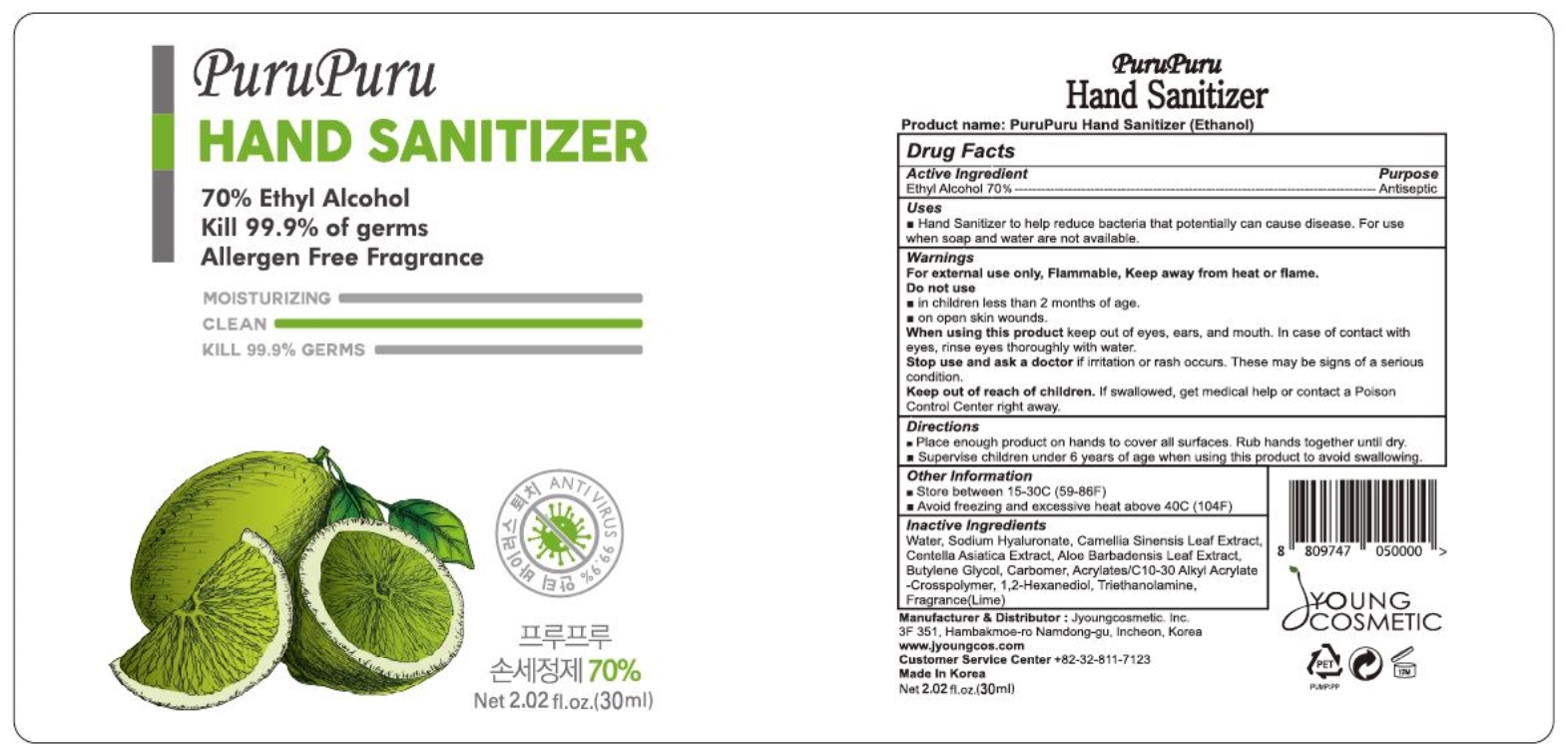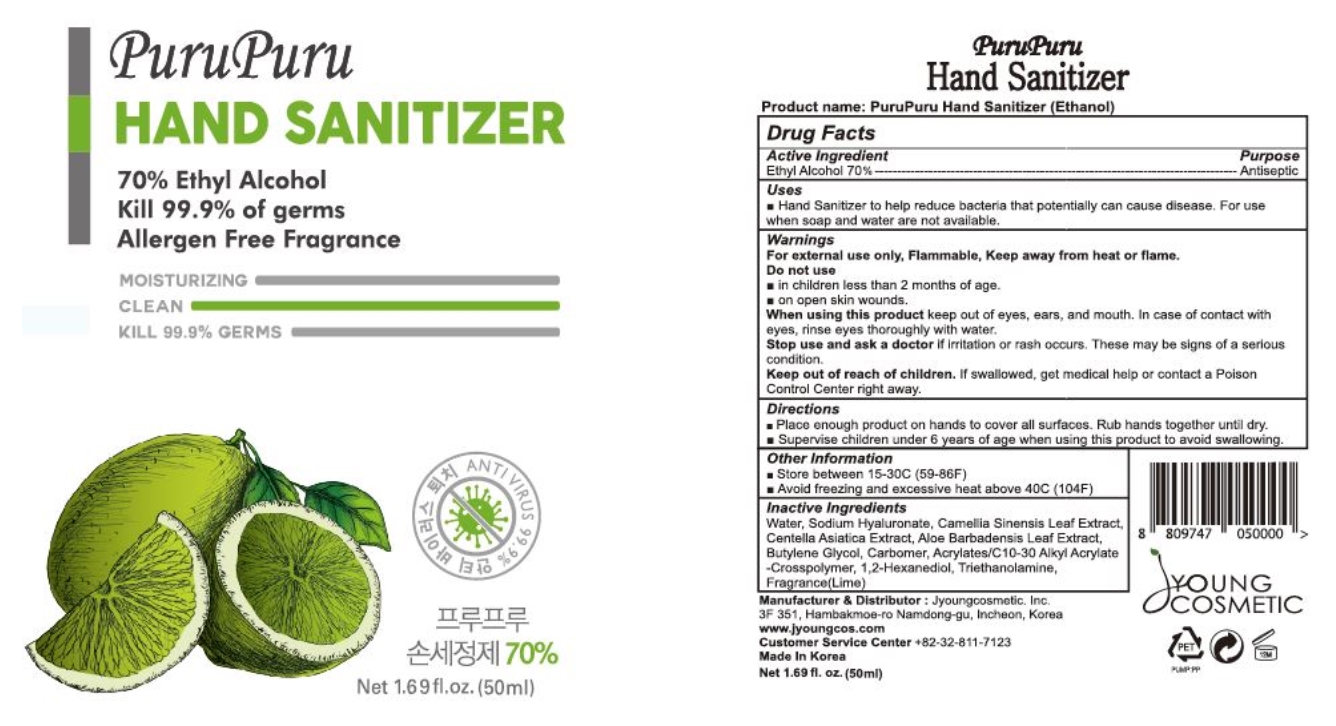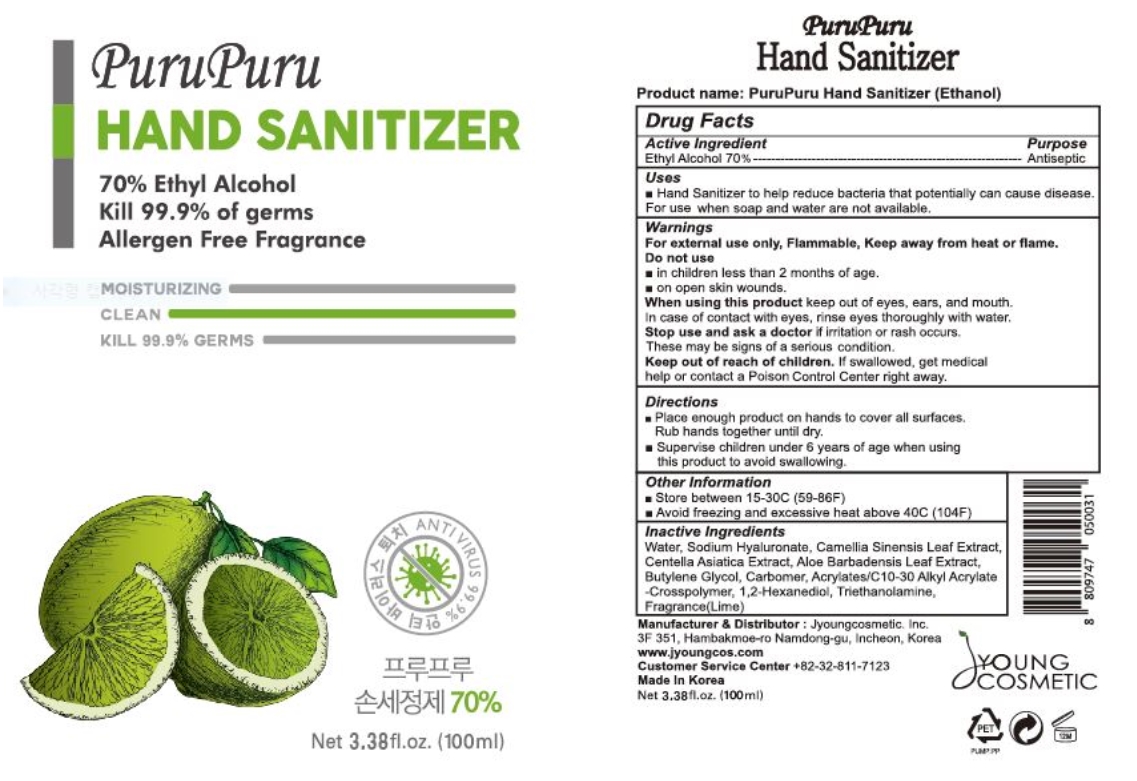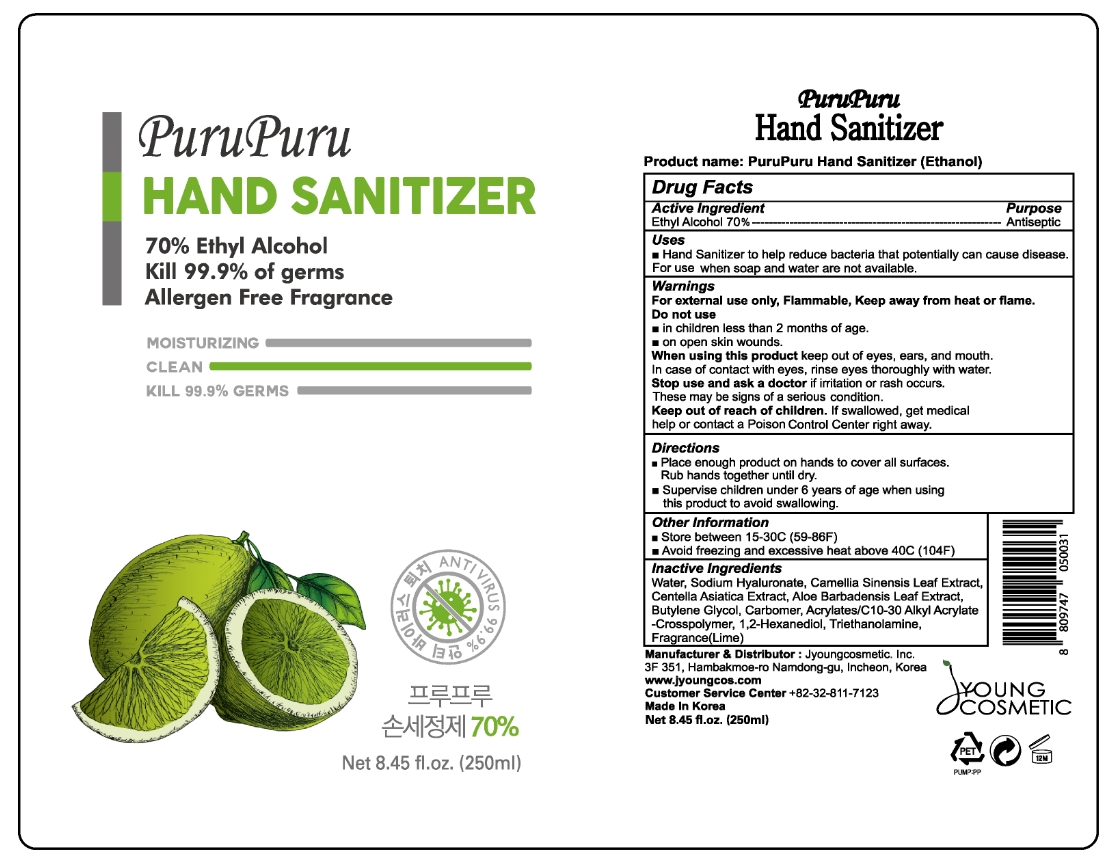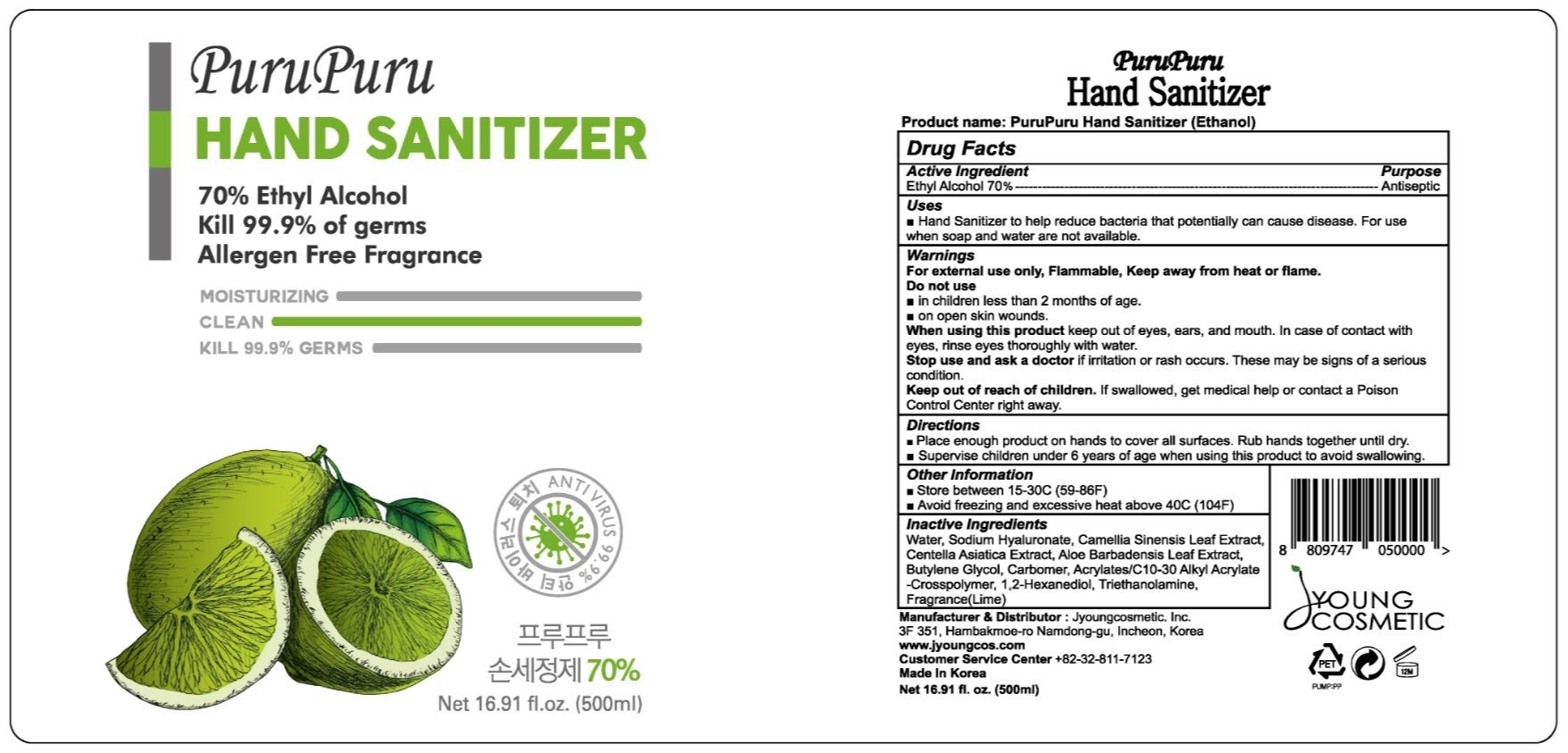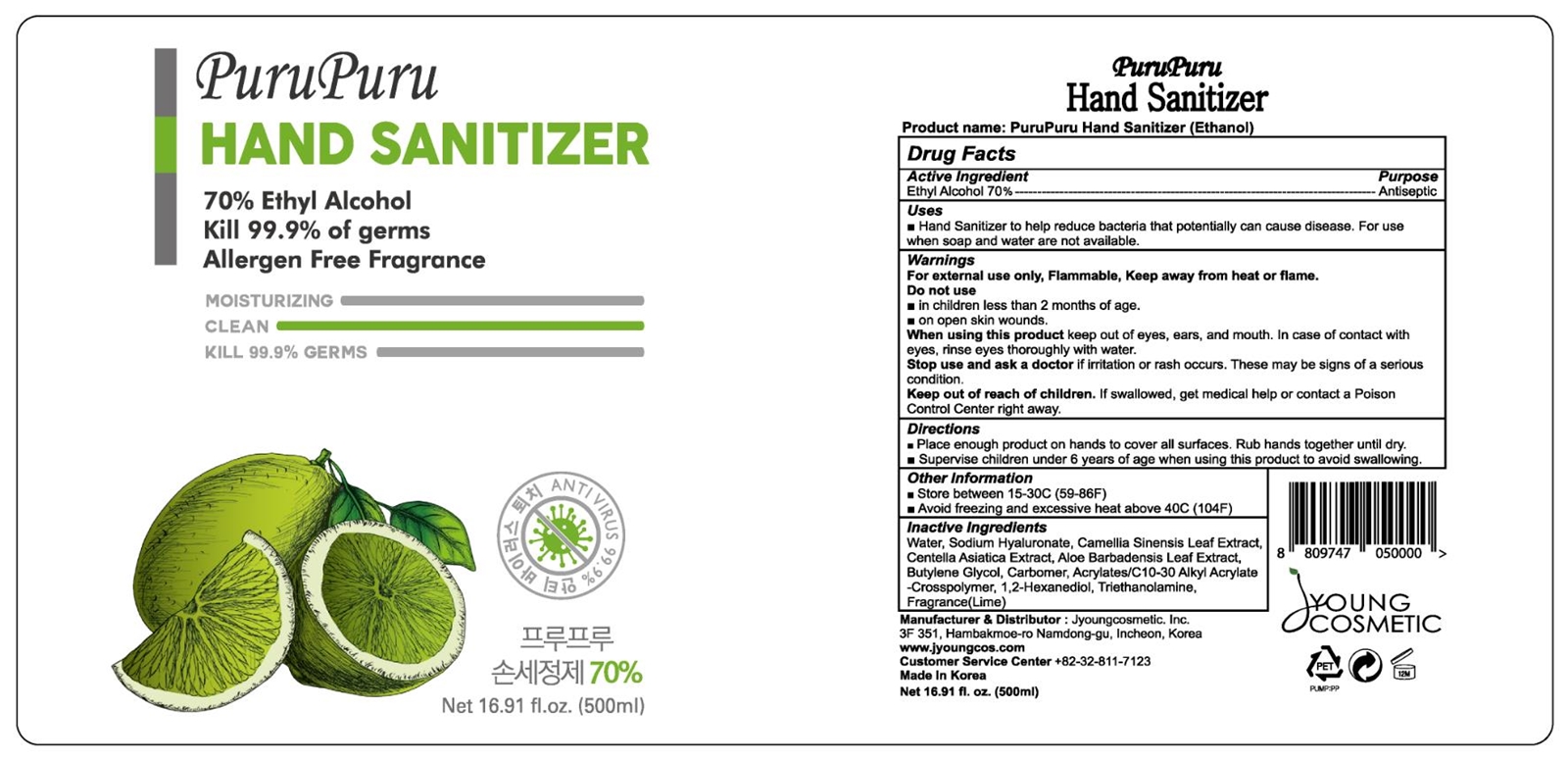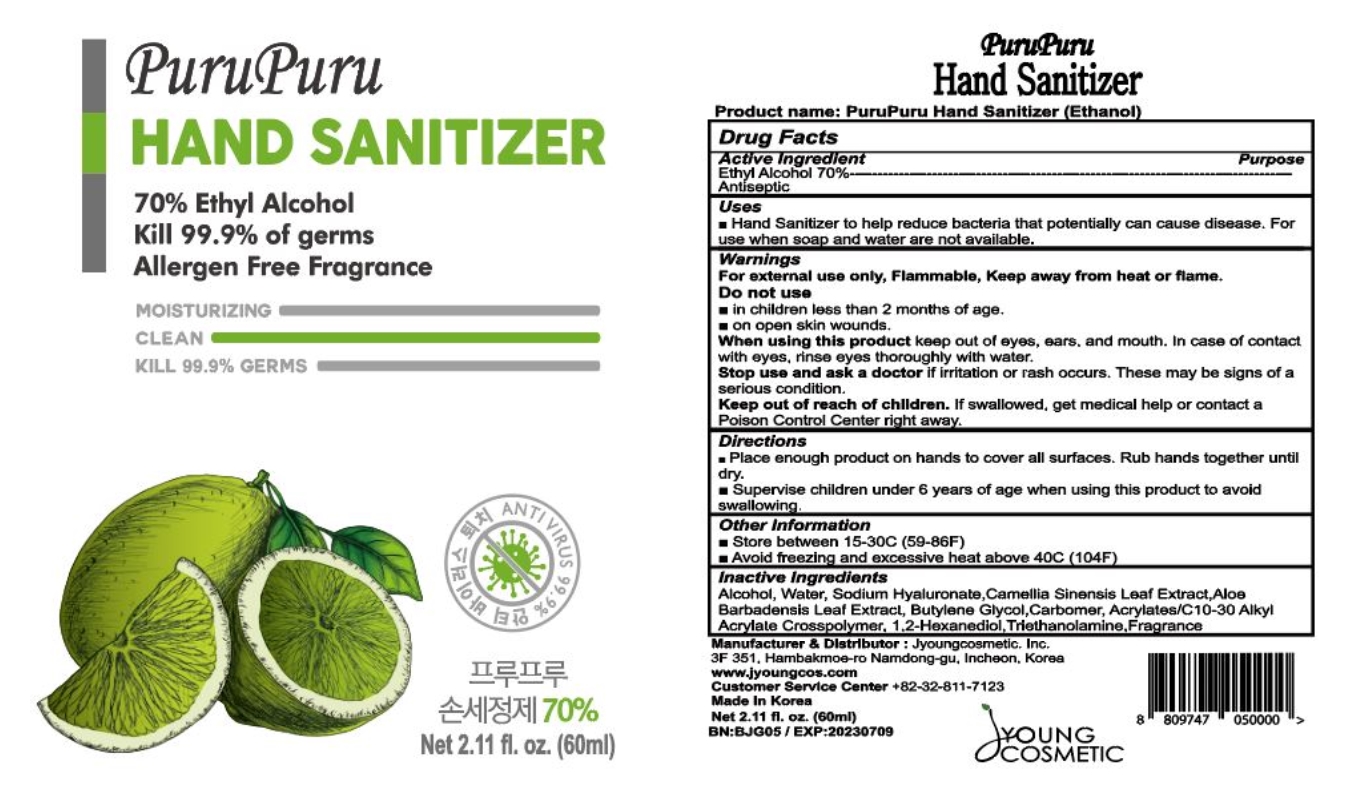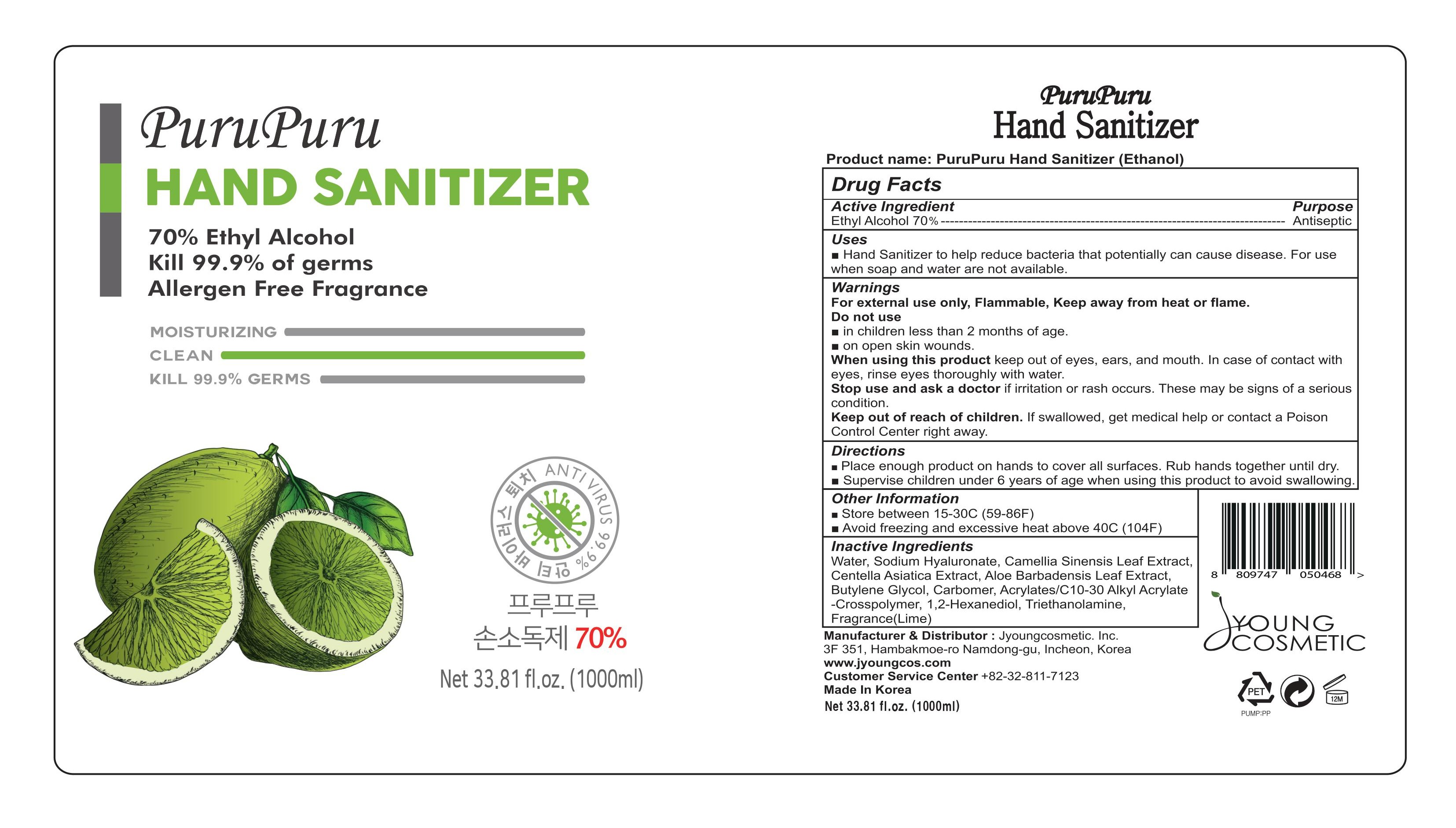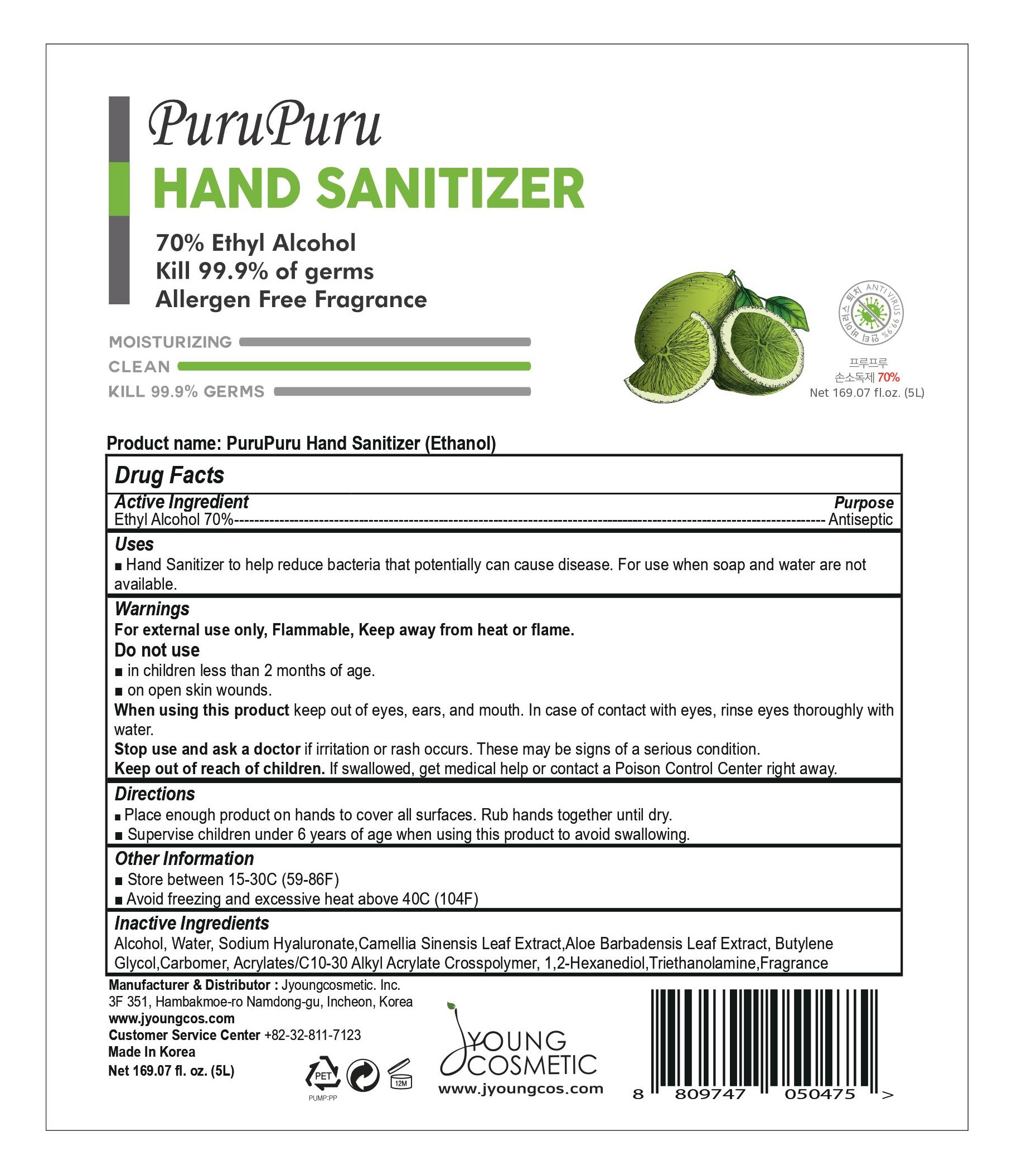 DRUG LABEL: PURUPURU HAND SANITIZER
NDC: 79547-201 | Form: GEL
Manufacturer: Jyoungcosmetic Inc.
Category: otc | Type: HUMAN OTC DRUG LABEL
Date: 20220121

ACTIVE INGREDIENTS: ALCOHOL 71.25 mL/100 mL
INACTIVE INGREDIENTS: TROLAMINE; HYALURONATE SODIUM; CENTELLA ASIATICA; BUTYLENE GLYCOL; CARBOMER INTERPOLYMER TYPE A (55000 CPS); 1,2-HEXANEDIOL; CARBOMER HOMOPOLYMER, UNSPECIFIED TYPE; WATER; GREEN TEA LEAF; ALOE VERA LEAF

79547-201

Active Ingredient

Ethyl Alcohol 70%

Purpose

Antiseptic

Uses

Hand Sanitizer to help reduce bacteria that potentially can cause disease. For use when soap and water are not available.

Warnings

For external use only, Flammable, Keep away from heat or flame.

Do not use

in children less than 2 months of age.

on open skin wounds.

When using this product

keep out of eyes, ears, and mouth. In case of contact with eyes, rinse eyes thoroughly with water.

Stop use and ask a doctor

if irritation or rash occurs. These may be signs of a serious condition.

Keep out of reach of children.

If swallowed, get medical help or contact a Posion Control Center right away.

Directions

Place enough product on hands to cover all surfaces. Rub hands together until dry.

Supervise children under 6 years of age when using this product to avoid swallowing.

Other information

Store between 15-30C (59-86F)

Avoid freezing and excessive heat above 40C (104F)

Inactive Ingredients

Water, Sodium Hyaluronate, Camellia Sinensis Leaf Extract, Centella Asiatica Extract, Aloe Barbadensis Leaf Extract, Butylene Glycol, Carbomer, Acrylates/C10-30 Alkyl Acrylate Crosspolymer, 1,2-Hexanediol, Triethanolamine, Fragrance (Lime)